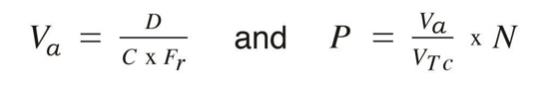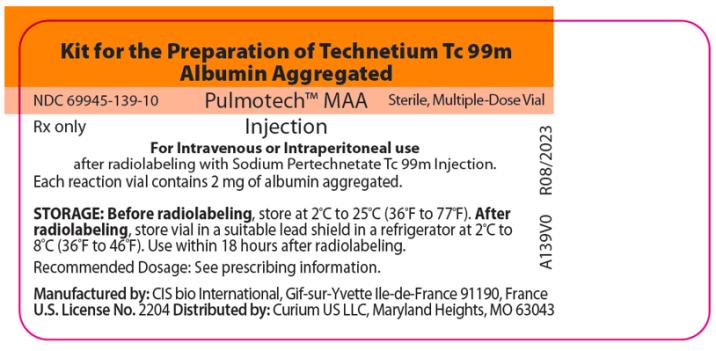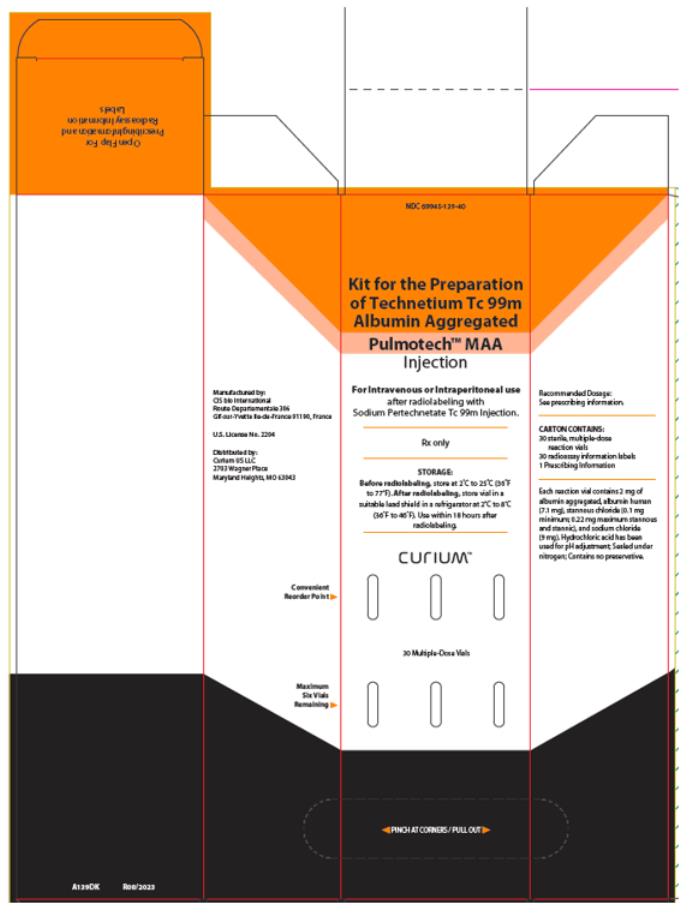 DRUG LABEL: Pulmotech MAA
NDC: 69945-139 | Form: INJECTION, POWDER, LYOPHILIZED, FOR SUSPENSION
Manufacturer: Curium US LLC
Category: prescription | Type: HUMAN PRESCRIPTION DRUG LABEL
Date: 20251013

ACTIVE INGREDIENTS: ALBUMIN AGGREGATED 2 mg/15 mL
INACTIVE INGREDIENTS: ALBUMIN HUMAN 7.1 mg/15 mL; STANNOUS CHLORIDE 0.1 mg/15 mL; SODIUM CHLORIDE 9 mg/15 mL

HIGHLIGHTS OF PRESCRIBING INFORMATION

These highlights do not include all the information needed to use PULMOTECH™ MAA safely and effectively. See full prescribing information for PULMOTECH MAA.
PULMOTECH MAA (kit for the preparation of technetium Tc 99m albumin aggregated) injection, for intravenous or intraperitoneal use.
Initial U.S. Approval: 2020

RECENT MAJOR CHANGES

Dosage and Administration, Directions for Drug Preparation and Handling (2.5) 10/2025

1 INDICATIONS AND USAGE

PULMOTECH MAA, after radiolabeling with technetium-99m is a radioactive diagnostic agent indicated for:

- Lung scintigraphy as an adjunct in the evaluation of pulmonary perfusion in adults and pediatric patients. (1)
- Peritoneovenous shunt scintigraphy as an aid in the evaluation of its patency in adults. (1)

2 DOSAGE AND ADMINISTRATION

- For lung perfusion scintigraphy, the following recommended activity is administered by intravenous injection.
  • Adults: 37 MBq to 148 MBq (1 mCi to 4 mCi) and 200,000 particles to 700,000 particles. (2.3)
  • Pediatric patients aged 4 weeks and older: 0.925 MBq/kg to 1.85 MBq/kg of body weight (0.025 mCi/kg to 0.05 mCi/kg); the minimum activity is 7.4 MBq (0.2 mCi). The number of particles will vary with age and body weight of the pediatric patient. (2.3)
  • Pediatric patients aged less than 4 weeks: 7.4 MBq to 18.5 MBq (0.2 mCi to 0.5 mCi); 10,000 particles to 50,000 particles. (2.3)
- For peritoneovenous shunts scintigraphy in adults: 37 MBq to 111 MBq (1 mCi to 3 mCi) and 200,000 particles to 700,000 particles by intraperitoneal injection. (2.4)
- See Full Prescribing Information for radiation safety, patient preparation, drug preparation, administration, imaging, and radiation dosimetry information. (2.1, 2.2, 2.5, 2.6, 2.7)

3 DOSAGE FORMS AND STRENGTHS

Kit for the preparation of Technetium Tc 99m Albumin Aggregated Injection: 2 mg of albumin aggregated as a lyophilized powder in a multiple-dose reaction vial. Upon radiolabeling, it provides a suspension of Technetium Tc 99m Albumin Aggregated Injection containing up to 6.85 MBq (185 mCi) in 2 to 13 mL volume at time of preparation. Each vial contains 2,000,000 to 4,000,000 particles. (3)

4 CONTRAINDICATIONS

- Severe pulmonary hypertension. (4)
- A history of hypersensitivity reactions to albumin human. (4)

5 WARNINGS AND PRECAUTIONS

- Patients with Pulmonary Hypertension: Administer the lowest number of particles possible and have emergency resuscitation equipment available. (5.1)
- Hypersensitivity Reactions: Have emergency resuscitation equipment and trained personnel available. Interrupt the administration if a reaction occurs during administration. Monitor patients. (5.2)
- Risk of Temporary Impediment to Blood Flow in Patients with Right-to-Left Heart Shunts: Administer the lowest possible number of particles. (5.3)
- Radiation Risks: Ensure safe handling to minimize radiation exposure to the patient and healthcare providers. (5.4)

6 ADVERSE REACTIONS

The following adverse reactions have been reported: Death in patients with severe pulmonary hypertension, anaphylaxis, impairment of cardiac and circulatory functions in the form of changes in respiration, pulse, and blood pressure, chest pain, and possible syncope, urticaria, reddening of the face, sweating, nausea, and injection site reaction. (6)

To report SUSPECTED ADVERSE REACTIONS, contact CURIUM US LLC at 1-866-789-2211 or FDA at 1-800-FDA-1088 or www.fda.gov/medwatch.

8 USE IN SPECIFIC POPULATIONS

Lactation: Temporarily discontinue breastfeeding. A lactating woman should pump and discard breastmilk for at least 24 hours after technetium Tc 99m albumin aggregated injection administration. (8.2)

FULL PRESCRIBING INFORMATION

1 INDICATIONS AND USAGE

PULMOTECH MAA, after radiolabeling with technetium-99m, is indicated for:

- Lung scintigraphy as an adjunct in the evaluation of pulmonary perfusion in adults and pediatric patients.
- Peritoneovenous shunt scintigraphy as an aid in the evaluation of its patency in adults.

2 DOSAGE AND ADMINISTRATION

2.1 Radiation Safety – Drug Handling

After radiolabeling of PULMOTECH MAA, the vial contains Technetium Tc 99m Albumin Aggregated Injection. Handle Technetium Tc 99m Albumin Aggregated Injection with appropriate safety measures to minimize radiation exposure [see Warnings and Precautions (5.4)]. Use waterproof gloves, effective radiation shielding, and other appropriate safety measures when preparing and handling Technetium Tc 99m Albumin Aggregated Injection.

Radiopharmaceuticals should be used by or under the control of healthcare providers who are qualified by specific training and experience in the safe use and handling of radionuclides, and whose experience and training have been approved by the appropriate governmental agency authorized to license the use of radionuclides.

2.2 Patient Preparation

Instruct patients to drink a sufficient amount of water to ensure adequate hydration prior to administration of Technetium Tc 99m Albumin Aggregated Injection and to continue to drink and void frequently following administration to reduce radiation exposure [see Warnings and Precautions (5.4)].

2.3 Recommended Dosage for Lung Perfusion Scintigraphy

Adult Patients

The recommended activity for lung perfusion scintigraphy in adult patients is 37 MBq to 148 MBq (1 mCi to 4 mCi) by intravenous injection.

The range of particle numbers per single injection should be 200,000 to 700,000 with the recommended number of approximately 350,000. Depending on the activity added and volume of the final radiolabeled product, the volume of the dose may vary from 0.2 mL to 1.9 mL.

The number of particles available per dose of Technetium Tc 99m Albumin Aggregated Injection will vary depending on the physical decay of technetium-99m that has occurred. The number of particles in any dose and volume to be administrated may be calculated as follows:

Where:

Va = volume to be administered in mL

D = desired activity to be administered in MBq (mCi)

C = concentration at calibration time of Sodium Pertechnetate Tc 99m Injection to be added to the reaction vial in MBq/mL (mCi/mL)

Fr = fraction of Technetium-99m remaining after the time of calibration from Table 6 [see Description (11.3)]

P = number of particles in dose to be administered

Va = volume to be administered in mL

VTc = volume of Sodium Pertechnetate Tc 99m Injection added to reaction vial in mL

N = number of particles per vial. The number of particles per vial for the lot is located on the vial label.

Pediatric Patients Aged 4 Weeks and Older

The recommended activity for lung perfusion scintigraphy in pediatric patients aged 4 weeks and older by intravenous injection is based on body weight and ranges from 0.925 MBq/kg to 1.85 MBq/kg (0.025 mCi/kg to 0.05 mCi/kg). The minimum recommended dose for lung perfusion scintigraphy in this age is 7.4 MBq (0.2 mCi).

The number of particles will vary with age and body weight of the pediatric patient. Particle numbers administered in four different age and weight categories are shown in Table 1.

Table 1 – Particle Numbers Administered in Four Different Age and Weight Categories of Pediatric Patients Receiving Maximum Recommended Activity of Technetium Tc 99m Albumin Aggregated Injection for Lung Perfusion Scintigraphy
Age |  |  | 15 years |  | 10 years |  | 5 years |  | 1 year
Weight (kg) |  |  | 55 |  | 33.5 |  | 20.3 |  | 12.1
Maximal recommended activity |  |  | MBq 103.6 | mCi 2.8 | MBq 62.9 | mCi 1.7 | MBq 37 | mCi 1 | MBq 22.2 | mCi 0.6
Range of particles administered |  |  | 200,000 to 700,000 |  | 200,000 to 300,000 |  | 200,000 to 300,000 |  | 50,000 to 150,000

Pediatric Patients Aged Less Than 4 Weeks (Neonates)

The recommended activity for lung perfusion scintigraphy in neonates by intravenous injection is 7.4 MBq to 18.5 MBq (0.2 mCi to 0.5 mCi). The number of particles in neonates for lung perfusion scintigraphy ranges from 10,000 to 50,000. Use the lowest possible number of particles for neonates.

2.4 Recommended Dosage for Peritoneovenous Shunt Scintigraphy in Adults

The recommended activity for peritoneovenous shunt scintigraphy in adult patients is 37 MBq to 111 MBq (1 mCi to 3 mCi) by intraperitoneal injection and the number of particles per single injection should be 200,000 to 700,000 with the recommended number of approximately 350,000. Depending on the activity added and volume of the final radiolabeled product, the volume of the dose may vary from 0.2 mL to 1.9 mL. For calculation of the number of particles to be administered, see Recommended Dosage for Lung Perfusion Scintigraphy in Adult Patients [see Dosage and Administration (2.3)]. Assure uniform mixing with peritoneal fluid.

Alternatively, administer the drug by percutaneous transtubal injection. The recommended activity for percutaneous transtubal administration in adult patients is 12 MBq to 37 MBq (0.3 mCi to 1 mCi) in a volume not to exceed 0.5 mL.

2.5 Directions for Drug Preparation and Handling

Procedural Precautions

- Perform all transfer and vial stopper entries using aseptic techniques.
- Wear waterproof gloves during the entire preparation procedure and during subsequent patient dose withdrawals from the PULMOTECH MAA vial.
- Make all transfers of Sodium Pertechnetate Tc 99m Injection during the preparation procedure with an adequately shielded syringe.
- Keep the prepared Technetium Tc 99m Albumin Aggregated Injection in the dispensing vial shield described below (with cap in place) during the useful life of the radioactive preparation. Make all withdrawals and injections of the Technetium Tc 99m Albumin Aggregated Injection with an adequately shielded syringe.

Procedure for the Preparation, Storage, and Handling of Technetium Tc 99m Albumin Aggregated Injection

1. If PULMOTECH MAA reaction vials are stored in the refrigerator, remove a vial and allow the contents to come to room temperature for approximately 5 minutes.
2. Remove the protective cap from the reaction vial and swab the rubber septum with an alcohol swab or a suitable bacteriostatic agent to disinfect the surface.
3. Place the vial in a suitable dispensing vial shield fitted with a shielded cap.
4. Calculate the amount of Sodium Pertechnetate Tc 99m Injection (2 mL to 13 mL) to be added to the reaction vial. In choosing the amount of Sodium Pertechnetate Tc 99m Injection to be used in the preparation of Technetium Tc 99m Albumin Aggregated Injection ensure that the radioactive dose will contain the desired number of macroaggregated albumin (MAA) particles, while taking into account the number of patients, administered activity, and radioactive decay. The recommended maximum activity of Sodium Pertechnetate Tc 99m Injection to be added to the reaction vial is 6.85 GBq (185 mCi). Calculate the amount of radioactivity per vial required to be added to maintain the number of particles per dose within a recommended range, for adults 200,000 to 700,000 and for pediatric patients as per Table 1 [see Dosage and Administration (2.3, 2.4)].
5. During or prior to addition of Sodium Pertechnetate Tc 99m Injection do not vent the reaction vial.
6. After adding Sodium Pertechnetate Tc 99m Injection to the reaction vial in the dispensing vial shield (with cap in place), mix the contents by inverting the vial at a frequency of one (1) inversion per second for 2 minutes (approximately 120 inversions total) and allow to stand for a minimum of 15 minutes at room temperature. Once prepared the product will have a turbid white appearance.
7. Assay the product in a suitable dose calibrator and record the total activity of Technetium Tc 99m Albumin Aggregated Injection, total volume, number of MAA particles, radioactive concentration, time and date of preparation, onto the radioassay information label and attach it to the dispensing vial shield. 0.9% Sodium Chloride Injection, USP may be used as a diluent for the radiolabeled product to achieve the desired number of particles and radioactivity.
8. Prior to withdrawing a dose, gently agitate the contents of the radiolabeled PULMOTECH MAA vial to resuspend any settled technetium Tc 99m albumin aggregated particles. Failure to mix the reaction vial contents adequately before use may result in a non-homogenous suspension with a resulting non-uniform distribution of radioactivity in the lung. Since the vials contain nitrogen to prevent oxidation of the complex, the vials should not be vented. If repeated withdrawals are made from the vial, the contents should not be replaced with air.
9. Store the radiolabeled PULMOTECH MAA in the dispensing vial shield in a refrigerator at 2°C to 8°C (36°F to 46°F). Use within 18 hours from the time of radiolabeling. Dispose unused radiolabeled PULMOTECH MAA in compliance with appropriate regulations.

2.6 Administration and Imaging Instructions

- Position the patient under the imaging apparatus before administration of Technetium Tc 99m Albumin Aggregated Injection because of rapid lung clearance of technetium Tc 99m albumin aggregated.
- Using proper shielding, visually inspect for foreign particulate matter and discoloration prior to administration. Do not administer if foreign particulates are found in the preparation.
- Mix the contents of the vial by gentle inversion just prior to withdrawing a patient dose.
- Withdraw the patient dose aseptically using a sterile needle (18 gauge to 21 gauge) and a shielded syringe.
- Measure the patient dose by a suitable radioactivity calibration system immediately prior to administration.
- Mix the contents of the syringe just before injection.
- Slow injection is recommended.
- If blood is drawn into the syringe, any unnecessary delay prior to injection may lead to clot formation.
- Begin lung imaging immediately after intravenous injection of the radiopharmaceutical. Due to high kidney uptake, imaging later than one-half hour after administration is not recommended.
- For peritoneovenous shunt imaging, obtain serial images of both the shunt and target organ.

2.7 Radiation Dosimetry

Intravenous Administration

Estimated radiation absorbed doses from intravenous administration are shown in Table 2.

Table 2. Estimated Radiation Absorbed Doses From Intravenous Administration of Technetium Tc 99m Albumin Aggregated Injection for Lung Perfusion Scintigraphy
Absorbed Dose per Activity Administered
(microGy/MBq)
Organs | Adults | 15 years | 10 years | 5 years | 1 year | Neonates
Total body | 4.05 | 3.96 | 7.63 | 8.38 | 13.5 | 32.4
Lungs | 59.5 | 74.3 | 138 | 157 | 297 | 1027
Liver | 4.86 | 11.6 | 28.6 | 16.8 | 27 | 75.7
Spleen | 4.59 | --* | -- | -- | -- | --
Kidneys | 2.97 | -- | -- | -- | -- | --
Bladder Wall 2 hour void 4.8 hour void No voiding intervals | 8.11 14.9 -- | -- -- 39.6 | -- 62 -- | -- 83.8 -- | 67.6 -- -- | 114 -- --
Testes 2 hour void 4.8 hour void No voiding intervals | 1.62 1.76 -- | -- -- 3.47 | -- -- 3.18 | -- -- 5.14 | -- -- 5.86 | -- -- 16.8
Ovaries 2 hour void 4.8 hour void No voiding intervals | 2.03 2.3 -- | -- -- 3.96 | -- -- 7 | -- -- 5.14 | -- -- 9.01 | -- -- 20.5

*--: Not available

Intraperitoneal Administration

Estimated radiation absorbed doses from intraperitoneal administration are shown in Table 3.

Table 3. Estimated Radiation Absorbed Doses From Intraperitoneal Administration of Technetium Tc 99m Albumin Aggregated Injection for Peritoneovenous Shunt Scintigraphy in Adults
Absorbed Dose per Activity Administered
(microGy/MBq)
Organs | Shunt Patency (Open) | Shunt Patency (Closed)
Lung | 62.2 | 15.1
Ovaries or Testes | 1.62 to 2.7 | 15.1
Organ in the Peritoneal Cavity | --* | 15.1
Total Body | 3.24 | 5.14

*--: Not available

3 DOSAGE FORMS AND STRENGTHS

Kit for the preparation of Technetium Tc 99m Albumin Aggregated Injection: 2 mg of albumin aggregated as a non-radioactive, white lyophilized powder in a multiple-dose reaction vial for radiolabeling with Sodium Pertechnetate Tc 99m Injection to prepare a suspension of Technetium Tc 99m Albumin Aggregated Injection containing up to 6.85 MBq (185 mCi) in 2 to 13 mL volume at time of preparation. Each vial contains 2,000,000 to 4,000,000 particles.

4 CONTRAINDICATIONS

PULMOTECH MAA is contraindicated in patients with:

- Severe pulmonary hypertension [see Warnings and Precautions (5.1)].
- A history of hypersensitivity to albumin human. Reactions have included anaphylaxis [see Warnings and Precautions (5.2)].

5 WARNINGS AND PRECAUTIONS

5.1 Patients with Pulmonary Hypertension

Deaths have been reported in patients with severe pulmonary hypertension after the administration of technetium Tc 99m albumin aggregated products [see Adverse Reactions (6)]. Assess patients for history or signs of pulmonary hypertension. PULMOTECH MAA is contraindicated in patients with severe pulmonary hypertension [see Contraindications (4)]. Administer the lowest number of particles possible, have emergency resuscitation equipment available, and monitor patients for adverse reactions.

5.2 Hypersensitivity Reactions

Serious hypersensitivity reactions including anaphylaxis have been reported in patients treated with products containing albumin human, including PULMOTECH MAA [see Adverse Reactions (6)]. Obtain a history of allergy or hypersensitivity reactions. PULMOTECH MAA is contraindicated in patients with a history of hypersensitivity to albumin human [see Contraindications (4)]. Have emergency resuscitation equipment and trained personnel available prior to administration of Technetium Tc 99m Albumin Aggregated Injection. Monitor all patients for hypersensitivity reactions.

5.3 Risk of Temporary Impediment to Blood Flow in Patients with Right-to-Left Heart Shunts

In patients with right-to-left heart shunts, risk for temporary mechanical impediment to blood flow may exist due to the rapid entry of aggregated albumin into the systemic circulation. Administer the lowest possible number of particles of Technetium Tc 99m Albumin Aggregated Injection in these patients.

5.4 Radiation Risks

Technetium Tc 99m albumin aggregated contributes to a patient’s overall long-term cumulative radiation exposure. Long-term cumulative radiation exposure is associated with an increased risk for cancer. Ensure safe handling to minimize radiation exposure to the patient and health care providers. Advise patients to hydrate before and after administration and to void frequently after administration [see Dosage and Administration (2.2)].

6 ADVERSE REACTIONS

The following clinically significant adverse reactions are described elsewhere in labeling:

- Patients with Pulmonary Hypertension [see Warnings and Precautions (5.1)].
- Hypersensitivity Reactions [see Warnings and Precautions (5.2)].

The following adverse reactions associated with the use of technetium Tc 99m albumin aggregated products including PULMOTECH MAA have been identified in clinical studies or postmarketing reports. Because these reactions are reported voluntarily from a population of uncertain size, it is not always possible to reliably estimate their frequency or establish a causal relationship to drug exposure.

Cardiovascular Disorders: Deaths in patients with severe pulmonary hypertension

Immune System Disorders: Hypersensitivity reactions such as anaphylaxis, impairment of cardiac and circulatory functions in the form of changes in respiration, pulse, and blood pressure, chest pain, and syncope, urticaria, reddening of the face, sweating, and nausea

Skin and Subcutaneous Tissue Disorders: Injection site reactions

8 USE IN SPECIFIC POPULATIONS

8.1 Pregnancy

Risk Summary

Available data from case reports on Technetium Tc 99m Albumin Aggregated Injection use are insufficient to evaluate drug-associated risks of major birth defects, miscarriage, or adverse maternal or fetal outcomes. Animal reproduction studies with technetium Tc 99m albumin aggregated have not been conducted. Although all radiopharmaceuticals have the potential to cause fetal harm depending on the fetal stage of development and the magnitude of the radiation dose, the radiation exposure to the fetus from technetium Tc 99m albumin aggregated is expected to be low (less than 0.50 mGy) (see Data).

The estimated background risk of major birth defects and miscarriage for the indicated population is unknown. All pregnancies have a background risk of birth defect, loss, or other adverse outcomes. In the U.S. general population, the estimated background risk of major birth defects and miscarriage in clinically recognized pregnancies is 2% to 4% and 15% to 20%, respectively.

Data

Human Data

No adverse fetal effects of radiation risks have been identified for diagnostic procedures involving less than 50 mGy, which represents less than 10 mGy fetal doses.

8.2 Lactation

Risk Summary

Technetium-99m is present in breast milk. There are no data on the effects of technetium Tc 99m albumin aggregated on the breastfed infant or the effects on milk production. PULMOTECH MAA is used for imaging in infants with lung disease; exposure to technetium-99m via breastmilk is expected to be lower. Based on clinical guidelines, exposure of technetium Tc 99m albumin aggregated to a breastfed infant may be minimized by advising a lactating woman to temporarily discontinue breastfeeding and to pump and discard breast milk for a minimum of at least 24 hours after administration of Technetium Tc 99m Albumin Aggregated Injection.

The developmental and health benefits of breastfeeding should be considered along with a mother’s clinical need for PULMOTECH MAA, any potential adverse effects on the breastfed child from technetium Tc 99m albumin aggregated or from the underlying maternal condition.

8.4 Pediatric Use

PULMOTECH MAA, after radiolabeling with technetium Tc-99m, is indicated for lung scintigraphy as an adjunct in the evaluation of pulmonary perfusion in pediatric patients (birth to less than 17 years of age). The safety profile of Technetium Tc99m Albumin Aggregated Injection is similar to the one in adults.

The safety and efficacy of PULMOTECH MAA have not been established for peritoneovenous shunt scintigraphy in pediatric patients.

8.5 Geriatric Use

No formal studies of PULMOTECH MAA in subjects aged 65 and over were performed to determine whether they respond differently from younger adult subjects. Other reported clinical experience has not identified differences in responses between the elderly and younger adult patients. In general, dose selection for an elderly patient should be cautious; administering the low end of the particle dosing range, reflecting the greater frequency of decreased hepatic, renal, or cardiac function, and of concomitant disease or other drug therapy.

11 DESCRIPTION

11.1 Product Characteristics

PULMOTECH MAA contains albumin aggregated obtained by fractionating material (source blood, plasma, serum, or placentas) from healthy human donors. The macroaggregated albumin (MAA) particles are formed by heat denaturation of stannous chloride treated albumin human under controlled conditions. Each vial contains 2,000,000 to 4,000,000 particles. The particle size distribution of the aggregated albumin is such that not less than 90% are 10 to 90 micrometers in size. There are no aggregated albumin particles greater than 150 micrometers in size as determined by circular equivalents.

PULMOTECH MAA (kit for the preparation of technetium Tc 99m albumin aggregated) injection provides a sterile, non-pyrogenic, non-radioactive, white lyophilized powder in a multiple-dose reaction vial, sealed under an atmosphere of nitrogen, for radiolabeling with Sodium Pertechnetate Tc 99m Injection to prepare Technetium Tc 99m Albumin Aggregated Injection, a radioactive diagnostic agent, for intravenous or intraperitoneal use.

Each reaction vial contains 2 mg of albumin aggregated, albumin human (7.1 mg), stannous chloride (0.1 mg minimum; 0.22 mg maximum stannous and stannic), sodium chloride (9 mg). Hydrochloric acid may have been added for pH adjustment. The pH is between 5 and 7. It contains no preservatives.

11.2 Physical Characteristics

Technetium-99m decays by isomeric transition with a physical half-life of 6.02 hours. The principal photon that is useful for detection and imaging is listed in Table 4.

Table 4 – Principal Radiation Emission Data for Technetium-99m
Radiation | Mean % per Disintegration | Energy (keV)
Gamma-2 | 89.07 | 140.5

11.3 External Radiation

The specific gamma ray constant for technetium-99m is 0.78 R/mCi-hr at 1 cm. The first half-value thickness of lead (Pb) for technetium-99m is 0.017 cm. A range of values for the relative attenuation of the radiation emitted by this radionuclide that results from interposition of various thicknesses of Pb is shown in Table 5. For example, the use of 0.25 cm of Pb will decrease the external radiation exposure by a factor of about 1,000.

Table 5 – Radiation Attenuation by Lead Shielding
Shield Thickness(Pb) cm | Coefficient of Attenuation
0.017 | 0.5
0.08 | 10-1
0.16 | 10-2
0.25 | 10-3
0.33 | 10-4

To correct for physical decay of this radionuclide, the fractions that remain at selected time intervals after the time of calibration are shown in Table 6.

Table 6– Physical Decay Chart for Technetium-99m, Half-Life 6.02 Hours
Hours | Fraction Remaining | Hours | Fraction Remaining
0* | 1.000 | 7 | 0.447
1 | 0.891 | 8 | 0.398
2 | 0.794 | 9 | 0.355
3 | 0.708 | 10 | 0.316
4 | 0.631 | 11 | 0.282
5 | 0.562 | 12 | 0.251
6 | 0.501

*Calibration Time

12 CLINICAL PHARMACOLOGY

12.1 Mechanism of Action

Within 1 to 5 minutes of intravenous injection, over 90 percent of the technetium Tc 99m albumin aggregated particles are trapped in the arterioles and capillaries of the lung.

Following intraperitoneal administration, technetium Tc 99m albumin aggregated mixes with the peritoneal fluid. Clearance from the peritoneal cavity varies from insignificant, which may occur with complete shunt blockage, to very rapid clearance with subsequent transfer into the systemic circulation when the shunt is patent.

12.2 Pharmacodynamics

The exposure-response relationship and time course of pharmacodynamic response for the safety and effectiveness of technetium Tc 99m albumin aggregated have not been fully characterized.

12.3 Pharmacokinetics

Distribution

Organ selectivity is a direct result of particle size. At 10 micrometer and below, the albumin aggregates are taken up by the reticuloendothelial system. Above 10 to 15 micrometer, the aggregates become lodged in the lung capillaries by a purely mechanical process. Distribution of aggregated albumin in the lungs is a function of regional pulmonary blood flow.

The albumin aggregated is sufficiently fragile for the capillary micro-occlusion to be temporary. Erosion and fragmentation reduce the particle size, allowing passage of the aggregates through the pulmonary alveolar capillary bed. The fragments then accumulate in the reticuloendothelial system.

Elimination

Elimination of the technetium Tc 99m albumin aggregated particles from the normal and abnormal human lungs occurs with a biological half-life of 10.8 hours (range 6.9 to 19 hours, n=5).

13 NONCLINICAL TOXICOLOGY

13.1 Carcinogenesis, Mutagenesis, Impairment of Fertility

No long-term animal studies have been performed to evaluate carcinogenic or mutagenic potential or whether technetium Tc 99m albumin aggregated affects fertility in males or females.

16 HOW SUPPLIED/STORAGE AND HANDLING

How Supplied

PULMOTECH MAA (kit for the preparation of technetium Tc 99m albumin aggregated) injection contains 2 mg of albumin aggregated as a white lyophilized powder in a multiple-dose reaction vial, sealed under an atmosphere of nitrogen, for radiolabeling with Sodium Pertechnetate Tc 99m Injection to prepare Technetium Tc 99m Albumin Aggregated Injection.

PULMOTECH MAA is supplied as:

- a carton (clam shell) of 5 vials (NDC 69945-139-20)
- a carton of 30 vials (NDC 69945-139-40)

Each 5-vial carton contains 5 multiple-dose reaction vials and 5 radioassay information labels. Each 30-vial carton contains 30 multiple-dose reaction vials and 30 radioassay information labels.

Storage and Handling

Before radiolabeling, store supplied reaction vials at 2°C to 25°C (36°F to 77ºF).

After radiolabeling with Sodium Pertechnetate Tc 99m Injection, store Technetium Tc 99m Albumin Aggregated Injection in a lead vial shield with cap in place, refrigerated at 2°C to 8°C (36°F to 46ºF) when not in use. Use within 18 hours after radiolabeling [see Dosage and Administration (2.5)].

Dispose unused Technetium Tc 99m Albumin Aggregated Injection in compliance with the appropriate regulations of the government agency authorized to license the use of this radionuclide.

This preparation is approved for use by persons under license by the Nuclear Regulatory Commission or the relevant regulatory authority of an Agreement State.

17 PATIENT COUNSELING INFORMATION

Adequate Hydration

Advise patients to drink a sufficient amount of water to ensure adequate hydration before their study and urge them to drink and urinate as often as possible during the first hours following the administration of Technetium Tc 99m Albumin Aggregated Injection in order to reduce radiation exposure [see Dosage and Administration (2.2)].

Pregnancy

Advise pregnant women of the risk of fetal exposure to radiation doses if they undergo a radionucleotide procedure [see Use in Specific Populations (8.1)].

Lactation

Advise a lactating woman to temporally discontinue breastfeeding and to pump and discard breast milk for 24 hours after Technetium Tc 99m Albumin Aggregated Injection administration to minimize radiation exposure to a breastfed infant [see Use in Specific Populations (8.2)].

Manufactured by:
CIS bio International
Route Departementale 306
Gif-sur-Yvette, Ile-de-France 91190, France

U.S License No. 2204

Distributed by:
Curium US LLC
2703 Wagner Place
Maryland Heights, MO 63043

©2025 Curium US LLC. Pulmotech™, Curium™, and the Curium logo are trademarks of a Curium company.

A139I0 Curium™

PRINCIPAL DISPLAY PANEL

Kit for the Preparation of Technetium Tc 99m Albumin Aggregated

NDC 69945-139-10 Pulmotech™ MAA Sterile, Multiple-Dose Vial

Rx only Injection

For Intravenous or Intraperitoneal use after radiolabeling with Sodium Pertechnetate Tc 99m Injection.

Each reaction vial contains 2 mg of albumin aggregated.

STORAGE: Before radiolabeling, store at 2°C to 25°C (36°F to 77°F). After radiolabeling, store vial in a suitable lead shield in a refrigerator at 2°C to 8°C (36°F to 46°F). Use within 18 hours after radiolabeling.

Recommended Dosage: See prescribing information.

Manufactured by: CIS bio International, Gif-sur-Yvette Ile-de-France 91190, France

U.S. License No. 2204 Distributed by: Curium US LLC, Maryland Heights, MO 63043

A139V0

R08/2023

PRINCIPAL DISPLAY PANEL

NDC 69945-139-40

Kit for the Preparation of Technetium Tc 99m Albumin Aggregated
Pulmotech™ MAA

Injection

For Intravenous or Intraperitoneal use after radiolabeling with Sodium Pertechnetate Tc 99m Injection.

Rx only

STORAGE:

Before radiolabeling, store at 2°C to 25°C (36°F to 77°F). After radiolabeling, store vial in a suitable lead shield in a refrigerator at 2°C to 8°C (36°F to 46°F). Use within 18 hours after radiolabeling.

CURIUM™

30 Multiple-Dose Vials

PINCH AT CORNERS / PULL OUT

Recommended Dosage: See prescribing information.

CARTON CONTAINS:

30 sterile, multiple-dose reaction vials

30 radioassay information labels

1 Prescribing Information

Each reaction vial contains 2 mg of albumin aggregated, albumin human (7.1 mg), stannous chloride (0.1 mg minimum; 0.22 mg maximum stannous and stannic), and sodium chloride (9 mg). Hydrochloric acid has been used for pH adjustment; Sealed under nitrogen; Contains no preservative.

Manufactured by:

CIS bio International

Route Departementale 306

Gif-sur-Yvette Ile-de-France 91190, France

U.S. License No. 2204

Distributed by:

Curium US LLC

2703 Wagner Place

Maryland Heights, MO 63043

Convenient Reorder Point

Maximum Six Vials Remaining

Open Flap For Prescribing Information and Radioassay Information Labels

A139DK

R08/2023